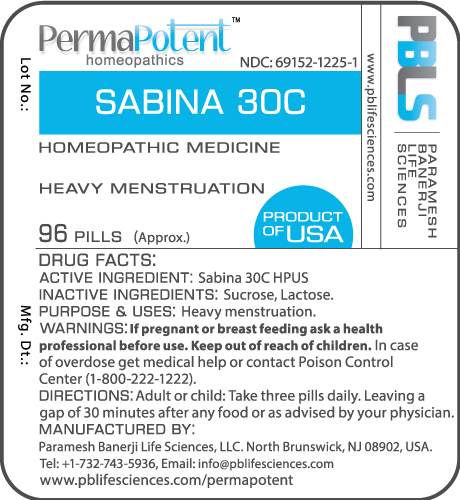 DRUG LABEL: Sabina 30C
NDC: 69152-1225 | Form: PELLET
Manufacturer: Paramesh Banerji Life Sciences LLC
Category: homeopathic | Type: HUMAN OTC DRUG LABEL
Date: 20160422

ACTIVE INGREDIENTS: JUNIPERUS SABINA LEAFY TWIG 30 [hp_C]/1 1
INACTIVE INGREDIENTS: SUCROSE; LACTOSE

DRUG FACTS: Active Ingredient

Sabina 30C HPUS

Inactive Ingredients

Sucrose, Lactose

Purpose

Heavy menstruation

Uses

Heavy menstruation

Warnings

If pregnant or breast feeding ask a health professional before use.

Keep out of reach of children. In case of overdose get medical help or contact a poison control center.

Direction

Adult or child: Take three pills daily. Leaving a gap of 30 minutes after any food or as advised by your physician

Manufactured by

Paramesh Banerji Life Sciences, LLC.

North Brunswick, NJ 08902, USA.

Principal Display Panel

NDC: 69152-1225-1
Sabina 30C
Homeopathic Medicine
Heavy menstruation
96 Pills (Approx.)
Product of USA